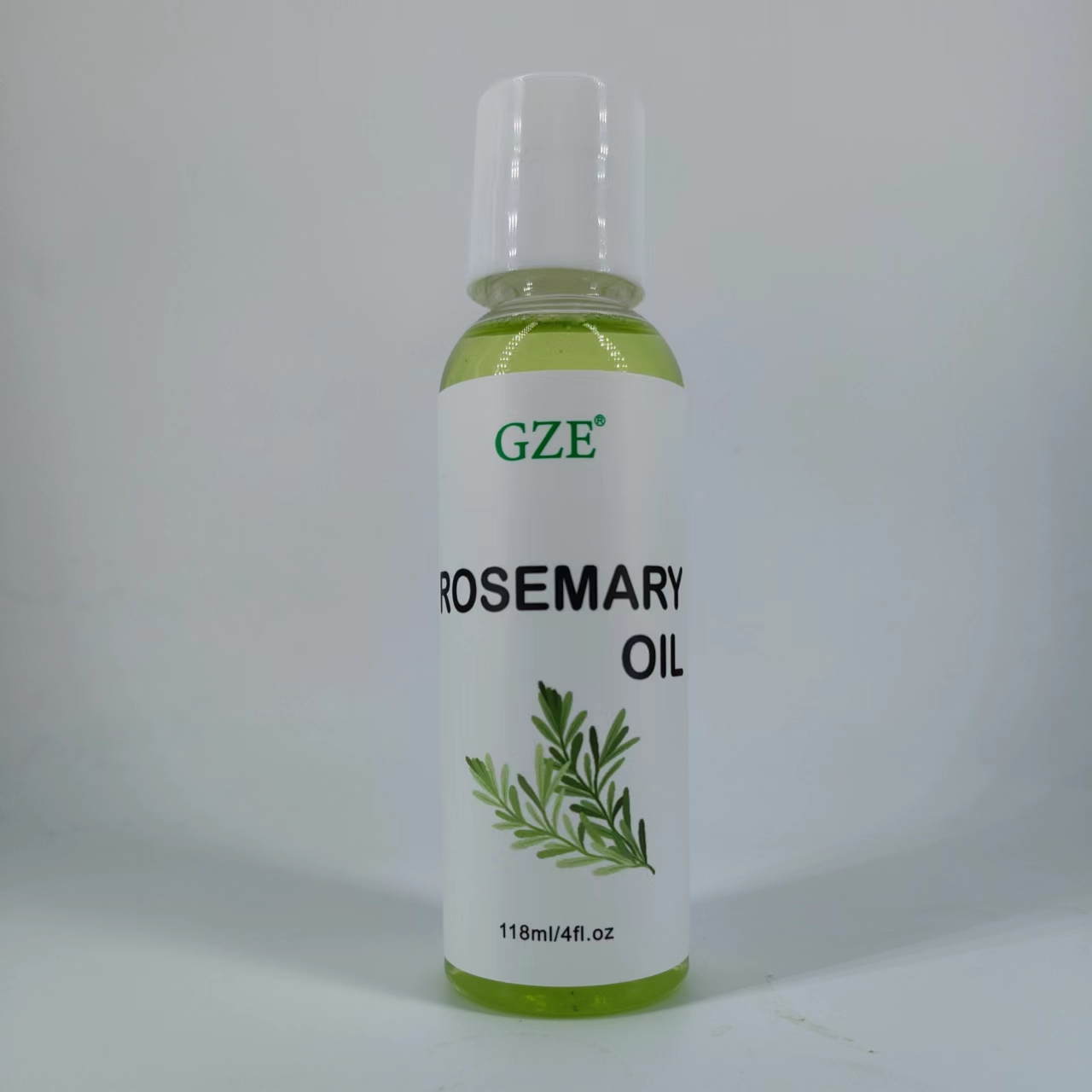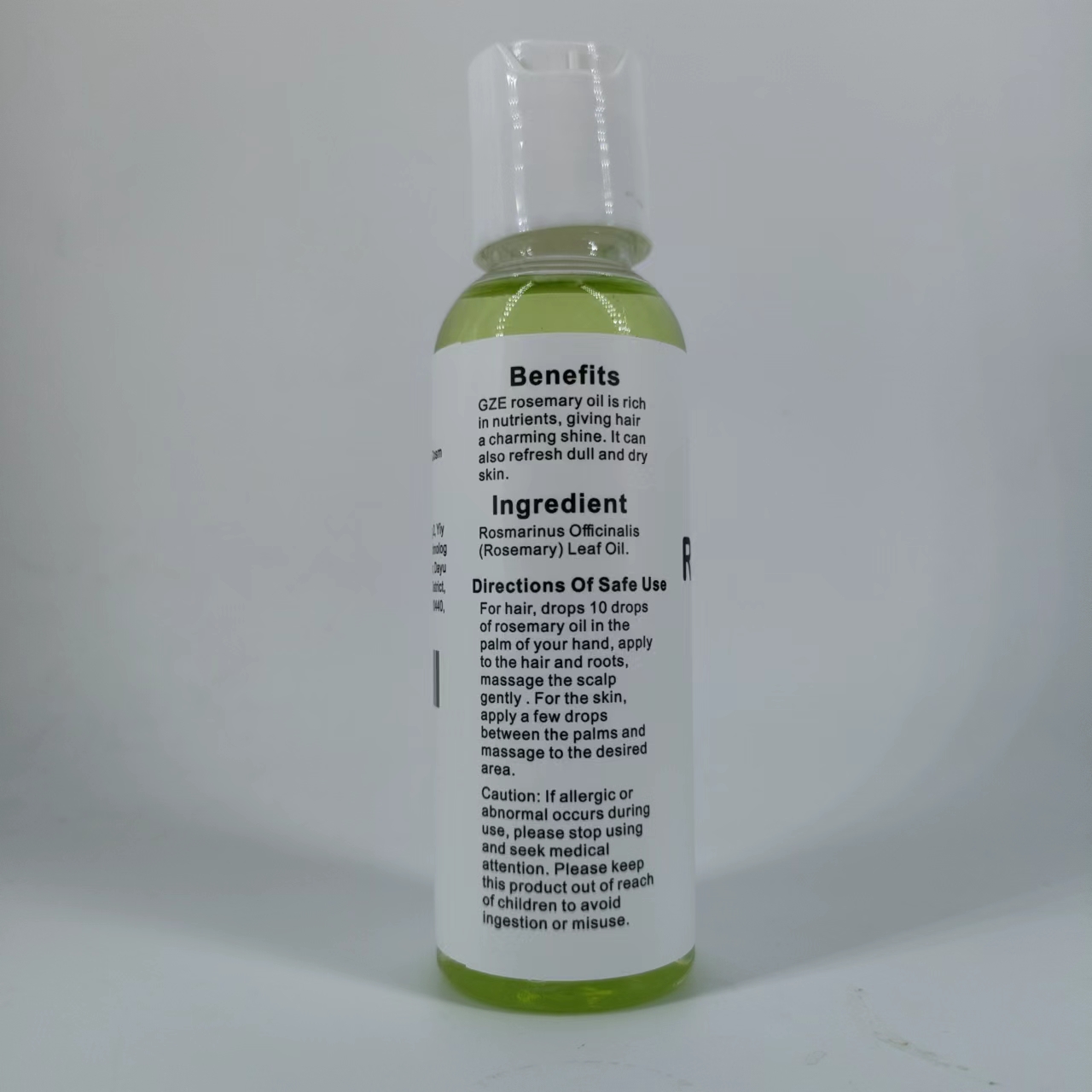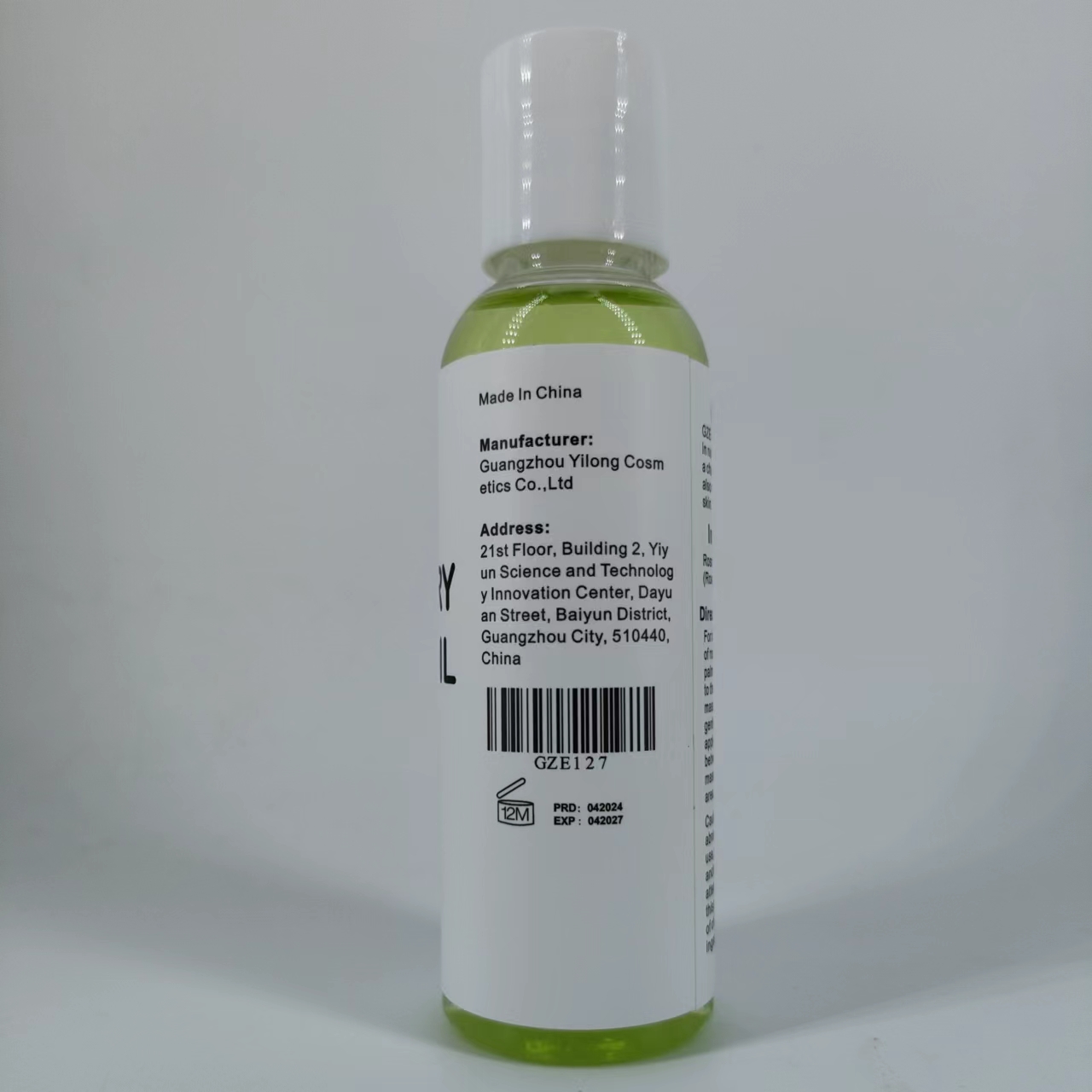 DRUG LABEL: GZE Rosemary Oil
NDC: 83566-127 | Form: OIL
Manufacturer: Guangzhou Yilong Cosmetics Co., Ltd
Category: otc | Type: HUMAN OTC DRUG LABEL
Date: 20240610

ACTIVE INGREDIENTS: ROSEMARY OIL 100 g/100 mL
INACTIVE INGREDIENTS: WATER

GZE Rosemary Oil

ACTIVE INGREDIENT

ROSEMARY OIL

PURPOSE

Moisturizes dry skin and hair.

INDICATIONS AND USAGE

For hair, drops 10 drops of rosemary oil in the palm of your hand, applyto the hair and roots,massage the scalp gently . For the skin,apply a few drops between the palms and massage to the desired areas.

WARNINGS

For external use only.

Stop use and ask a doctor if rash occurs.

Do not use on damaged or broken skin.

When using this product keep out of eyes. Rinse with water to remove.

Keep out of reach of children. If swallowed, get medical help or contact a Poison Control Center right away.

DOSAGE AND ADMINISTRATION

For hair, drops 10 dropsof rosemary oil in the palm of your hand, apply to the hair and roots,massage the scalp gently . For the skin,apply a few drops between the palms and massage to the desired area.

INACTIVE INGREDIENT

water